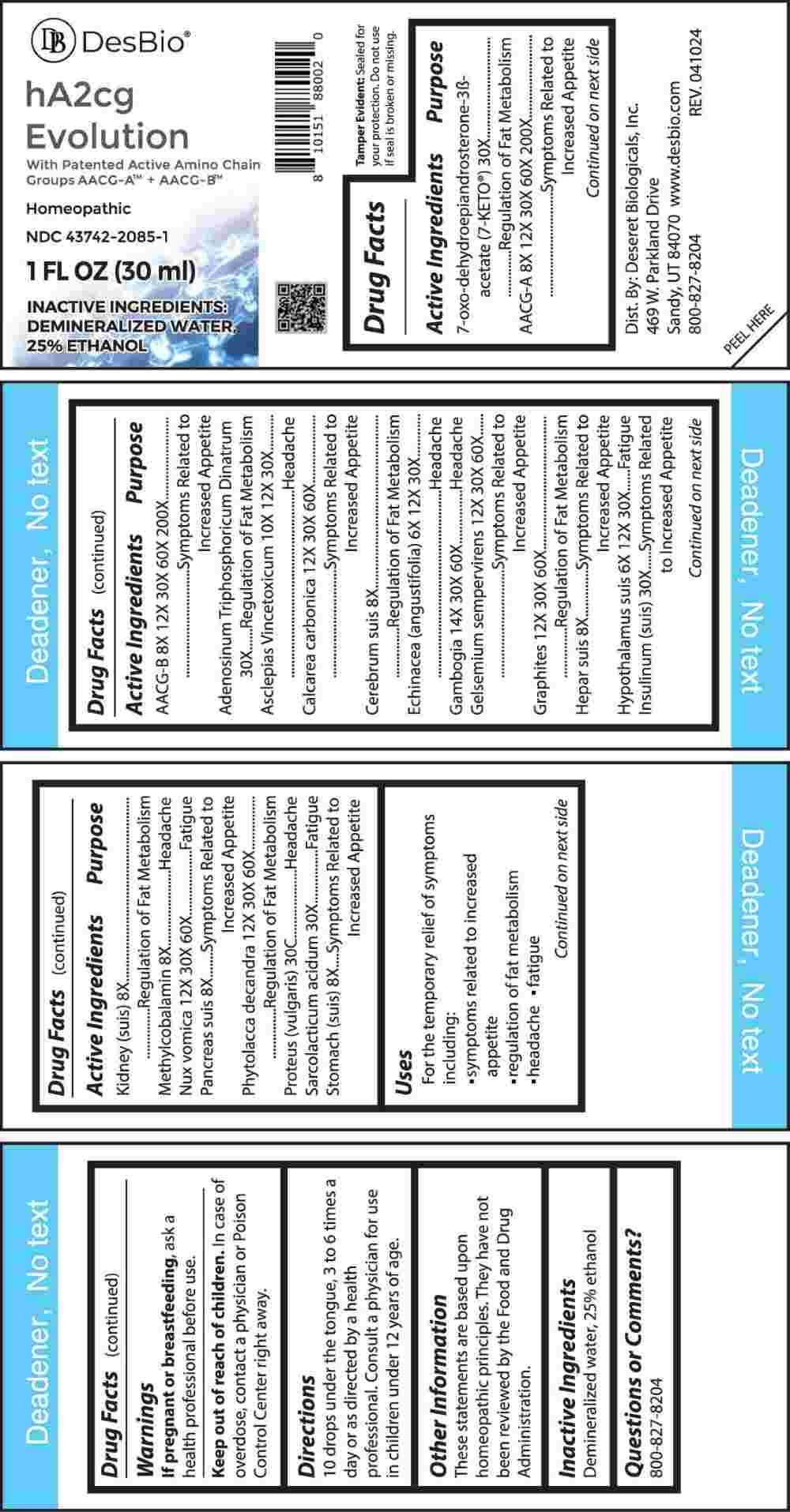 DRUG LABEL: HA2CG Evolution
NDC: 43742-2085 | Form: LIQUID
Manufacturer: Deseret Biologicals, Inc.
Category: homeopathic | Type: HUMAN OTC DRUG LABEL
Date: 20240814

ACTIVE INGREDIENTS: 7-OXODEHYDROEPIANDROSTERONE 3-ACETATE 30 [hp_X]/1 mL; APC-356433 8 [hp_X]/1 mL; APC-356434 8 [hp_X]/1 mL; ADENOSINE TRIPHOSPHATE DISODIUM 30 [hp_X]/1 mL; VINCETOXICUM HIRUNDINARIA ROOT 10 [hp_X]/1 mL; OYSTER SHELL CALCIUM CARBONATE, CRUDE 12 [hp_X]/1 mL; SUS SCROFA CEREBRUM 12 [hp_X]/1 mL; ECHINACEA ANGUSTIFOLIA WHOLE 6 [hp_X]/1 mL; GAMBOGE 14 [hp_X]/1 mL; GELSEMIUM SEMPERVIRENS ROOT 12 [hp_X]/1 mL; GRAPHITE 12 [hp_X]/1 mL; PORK LIVER 8 [hp_X]/1 mL; SUS SCROFA HYPOTHALAMUS 6 [hp_X]/1 mL; INSULIN PORK 30 [hp_X]/1 mL; PORK KIDNEY 8 [hp_X]/1 mL; METHYLCOBALAMIN 8 [hp_X]/1 mL; STRYCHNOS NUX-VOMICA SEED 12 [hp_X]/1 mL; SUS SCROFA PANCREAS 8 [hp_X]/1 mL; PHYTOLACCA AMERICANA ROOT 12 [hp_X]/1 mL; PROTEUS VULGARIS 30 [hp_C]/1 mL; LACTIC ACID, L- 30 [hp_X]/1 mL; SUS SCROFA STOMACH 8 [hp_X]/1 mL
INACTIVE INGREDIENTS: WATER; ALCOHOL

DRUG FACTS:

ACTIVE INGREDIENTS:

7-Oxo-Dehydroepiandrosterone 3-Acetate 30X, AACG-A 8X, 12X, 30X, 60X, 200, AACG-B 8X, 12X, 30X, 60X, 200, Adenosinum Triphosphoricum Dinatrum 30X, Asclepias Vincetoxicum 10X, 12X, 30X, Calcarea Carbonica 12X, 30X, 60X, Cerebrum Suis 8X, Echinacea (Angustifolia) 6X, 12X, 30X, Gambogia 14X, 30X, 60X, Gelsemium Sempervirens 12X, 30X, 60X, Graphites 12X, 30X, 60X, Hepar Suis 8X, Hypothalamus (Suis) 6X, 12X, 30X, Insulinum (Suis) 30X, Kidney (Suis) 8X, Methylcobalamin 8X, Nux Vomica 12X, 30X, 60X, Pancreas Suis 8X, Phytolacca Decandra 12X, 30X, 60X, Proteus (Vulgaris) 30C, Sarcolacticum Acidum 30X, Stomach (Suis) 8X.

PURPOSE:

7-Oxo-Dehydroepiandrosterone 3-Acetate – Regulation of Fat Metabolism , AACG-A – Symptoms Related to Increased Appetite, AACG-B 8X - Symptoms Related to Increased Appetite, Adenosinum Triphosphoricum Dinatrum - Regulation of Fat Metabolism, Asclepias Vincetoxicum - Headache, Calcarea Carbonica – Symptoms Related to Increased Appetite, Cerebrum Suis – Regulation of Fat Metabolism, Echinacea (Angustifolia) - Headache, Gambogia - Headache, Gelsemium Sempervirens – Symptoms Related to Increased Appetite, Graphites – Regulation of Fat Metabolism, Hepar Suis – Symptoms Related to Increased Appetite, Hypothalamus Suis - Fatigue, Insulinum (Suis) – Symptoms related to Increased Appetite, Kidney (Suis) – Regulation of Fat Metabolism, Methylcobalamin - Headache, Nux Vomica - Fatigue, Pancreas Suis – Symptoms Related to Increased Appetite, Phytolacca Decandra – Regulation of Fat Metabolism, Proteus (Vulgaris) - Headache, Sarcolacticum Acidum - Fatigue, Stomach (Suis) – Symptoms Related to Increased Appetite

USES:

For the temporary relief of symptoms including:

• symptoms related to increased appetite

• regulation of fat metabolism

• headache • fatigue

These statements are based upon homeopathic principles. They have not been reviewed by the Food and Drug Administration.

WARNINGS:

If pregnant or breast-feeding, ask a health professional before use.

Keep out of reach of children. In case of overdose, contact a physician or Poison Control Center right away.

Tamper Evident: Sealed for your protection. Do not use if seal is broken or missing.

KEEP OUT OF REACH OF CHILDREN:

In case of overdose, contact a physician or Poison Control Center right away.

DIRECTIONS:

10 drops under the tongue, 3 to 6 times a day or as directed by a health professional. Consult a physician for use in children under 12 years of age.

INACTIVE INGREDIENTS:

demineralized water, 25% ethanol

QUESTIONS:

Dist. By: Deseret Biologicals, Inc.
469 W. Parkland Drive

Sandy, UT 84070

www.desbio.com

800-827-8204

PACKAGE LABEL DISPLAY:

DesBio

hA2cg Evolution

With Patented Active Amino Chain

Groups AACG-A + AACG-B

Homeopathic
NDC 43742-2085-1

1 FL OZ (30 ml)